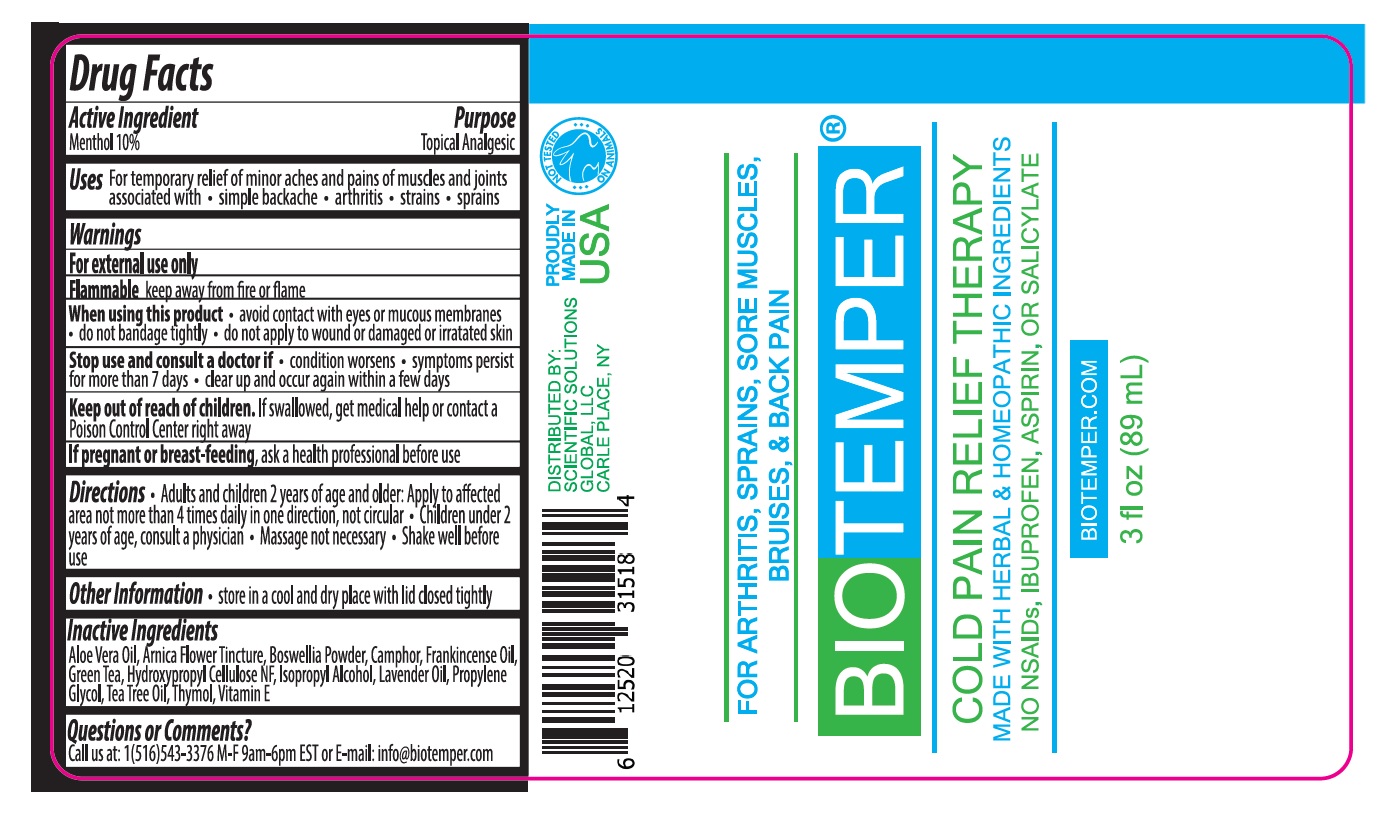 DRUG LABEL: BioTemper
NDC: 71718-111 | Form: LIQUID
Manufacturer: Scientific Solutions Global Llc
Category: otc | Type: HUMAN OTC DRUG LABEL
Date: 20200207

ACTIVE INGREDIENTS: MENTHOL, UNSPECIFIED FORM 10 g/100 mL
INACTIVE INGREDIENTS: ALOE VERA LEAF; ARNICA MONTANA WHOLE; FRANKINCENSE; CAMPHOR (SYNTHETIC); FRANKINCENSE OIL; GREEN TEA LEAF; HYDROXYPROPYL CELLULOSE, UNSPECIFIED; ISOPROPYL ALCOHOL; LAVENDER OIL; PROPYLENE GLYCOL; TEA TREE OIL; THYMOL; .ALPHA.-TOCOPHEROL

BIOTEMPER

Active Ingredient

Menthol 10%

Purpose

Topical Analgesic

Uses

For temporary relief of minor aches and pains of muscles and joints associated with • simple backache • arthritis • strains • sprains

Warnings

For external use only
Flammable keep away from fire or flame
When using this product • avoid contact with eyes or mucous membranes • do not bandage tightly • do not apply to wound or damaged or irritated skin
Stop use and consult a doctor if • condition worsens • symptoms persist for more than 7 days • clear up and occur again within a few days

If pregnant or breast-feeding, ask a health professional before use

Keep out of reach of children. If swallowed, get medical help or contact a Poison Control Center right away

Directions

• Adults and children 2 years of age and older: Apply to affected area not more than 4 times daily in one direction, not circular. • Children under 2 years of age, consult a physician • Massage not necessary • Shake well before use

Inactive Ingredients

Aloe Vera Oil, Arnica Flower Tincture, Boswellia Powder, Camphor, Frankincense Oil, Green Tea, Hydroxypropyl Cellulose NF, Isopropyl Alcohol, Lavender Oil, Propylene Glycol, Tea Tree Oil, Thymol, Vitamin E

Other Information

• store in a cool and dry place with lid closed tightly

Questions or Comments?

Call us at: 1(516)543-3376 M-F 9am-6pm EST or E-mail:info@biotemper.com

FOR ARTHRITIS, SPRAINS, SORE MUSCLES, BRUISES, & BACK PAIN

MADE WITH HERBAL & HOMEOPATHIC INGREDIENTS

NO NSAIDs, IBUPROFEN, ASPIRIN, OR SALICYLATE

BIOTEMPER.COM

DISTRIBUTED BY:

SCIENTIFIC SOLUTIONS GLOBAL, LLC

CARLE PLACE, NY

PROUDLY MADE IN USA